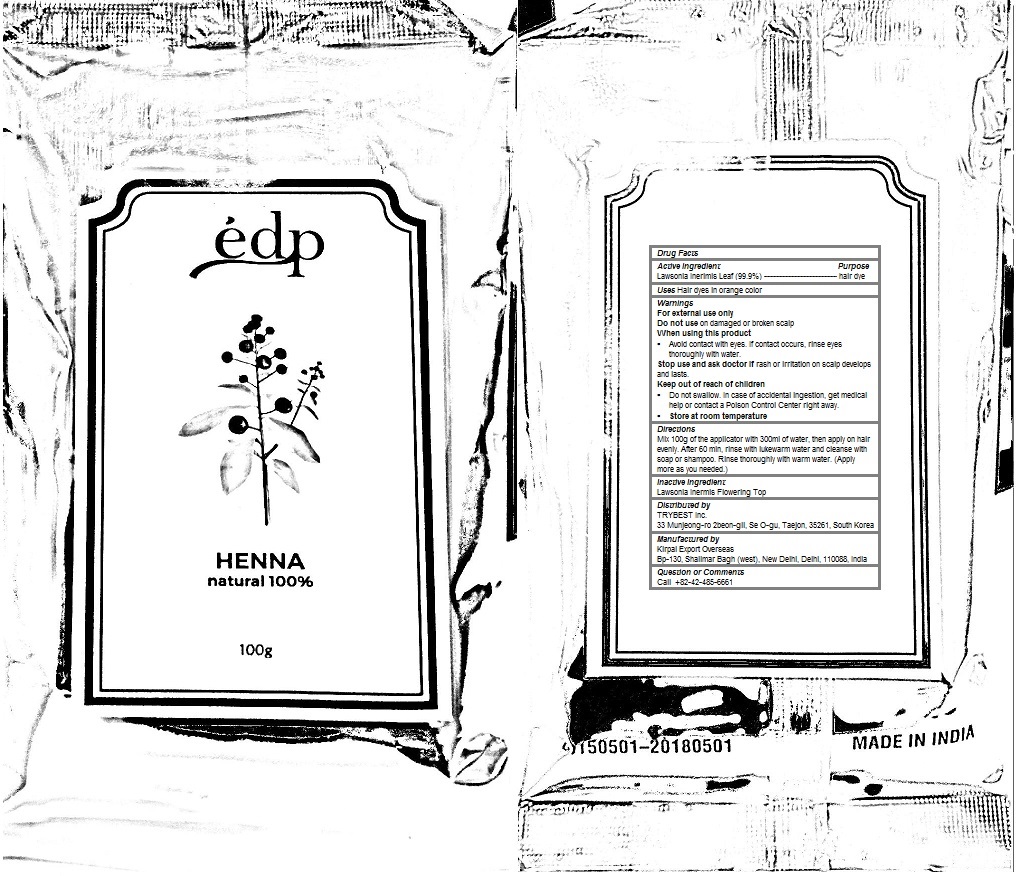 DRUG LABEL: EDP HENNA
NDC: 70434-101 | Form: POWDER
Manufacturer: TRYBEST Inc.
Category: otc | Type: HUMAN OTC DRUG LABEL
Date: 20190115

ACTIVE INGREDIENTS: LAWSONIA INERMIS LEAF 0.999 1/100 g
INACTIVE INGREDIENTS: LAWSONIA INERMIS FLOWERING TOP 0.001 1/100 g

EDP HENNA